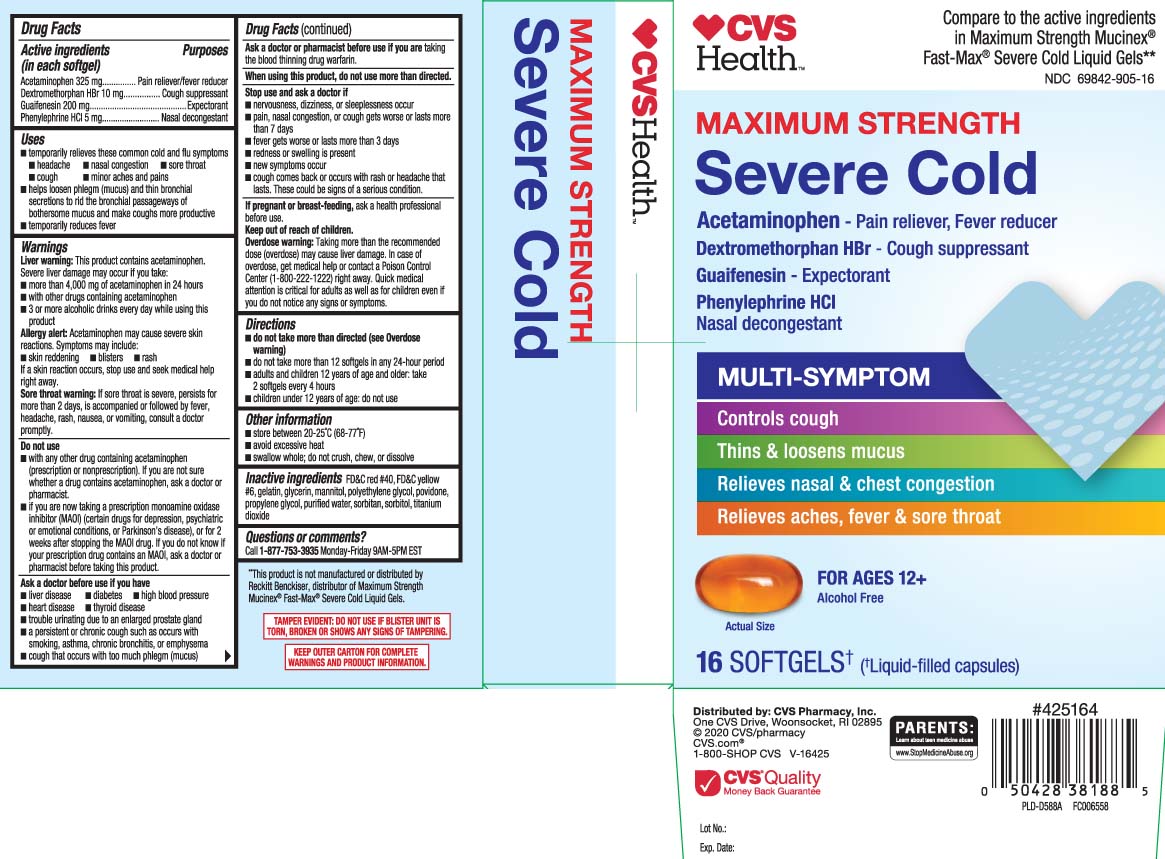 DRUG LABEL: Severe Cold
NDC: 69842-505 | Form: CAPSULE
Manufacturer: CVS Pharmacy
Category: otc | Type: HUMAN OTC DRUG LABEL
Date: 20250820

ACTIVE INGREDIENTS: ACETAMINOPHEN 325 mg/1 1; DEXTROMETHORPHAN HYDROBROMIDE 10 mg/1 1; GUAIFENESIN 200 mg/1 1; PHENYLEPHRINE HYDROCHLORIDE 5 mg/1 1
INACTIVE INGREDIENTS: MANNITOL; FD&C YELLOW NO. 6; FD&C RED NO. 40; GLYCERIN; GELATIN; PROPYLENE GLYCOL; WATER; POLYETHYLENE GLYCOL, UNSPECIFIED; POVIDONE; SORBITOL; SORBITAN; TITANIUM DIOXIDE

Drug Facts

Active ingredients (in each softgels)

Acetaminophen 325 mg

Dextromethorphan HBr 10 mg

Guaifenesin 200 mg

Phenylephrine HCl 5 mg

Purposes

Pain reliever/fever reducer

Cough suppressant

Expectorant

Nasal decongestant

Uses

- temporarily relieves these common cold and flu symptoms:
  - headache
  - nasal congestion
  - sore throat
  - cough
  - minor ache and pain
- temporarily reduces fever
- helps loosen phlegm (mucus) and thin bronchial secretions to rid the bronchial passageways of bothersome mucus and make coughs more productive

Warnings

Liver warning: This product contains acetaminophen. Severe liver damage may occur if you take:

- more than 4,000 mg of acetaminophen in 24 hours
- with other drugs containing acetaminophen
- 3 or more alcoholic drinks every day while using this product

Allergy alert: Acetaminophen may cause severe skin reactions. Symptoms may include:

- skin reddening
- blisters
- rash

If a skin reaction occurs, stop use and seek medical help right away.

Sore throat warning: If sore throat is severe, persists for more than 2 days, is accompanied or followed by fever, headache, rash, nausea or vomiting, consult a doctor promptly.

Do not use

- with any other drug containing acetaminophen (prescription or nonprescription). If you are not sure whether a drug contains acetaminophen, ask a doctor or pharmacist.
- if you are now taking a prescription monoamine oxidase inhibitor (MAOI) (certain drugs for depression, psychiatric or emotional conditions, or Parkinson's disease), or for 2 weeks after stopping the MAOI drug. If you do not know if your prescription drug contains an MAOI, ask a doctor or pharmacist before taking this product.

Ask a doctor before use if you have

- liver disease
- diabetes
- high blood pressure
- heart disease
- thyroid disease
- trouble urinating due to an enlarged prostate gland
- persistent or chronic cough such as occurs with smoking asthma , chronic bronchitis, or emphysema
- cough that occurs with too much phlegm(mucus)

Ask a doctor or pharmacist before use if you are

are taking the blood thinning drug warfarin

When using this product

do not use more than directed

Stop use and ask a doctor if

- nervousness, dizziness, or sleeplessness occur
- pain, nasal congestion, or cough gets worse, or lasts more than 7 days
- fever gets worse, or lasts more than 3 days
- redness or swelling is present
- new symptoms occur
- cough comes back, or occurs with fever, rash, or headache that lasts. These could be signs of a serious condition,

If pregnant or breast-feeding,

ask a health professional before use.

Keep out of reach of children.

Overdose warning: Taking more than the recommended dose (overdose) may cause liver damage. In case of overdose, get medical help or contact a Poison Control Center (1-800-222-1222) right away. Quick medical attention is critical for adults as well as for children even if you do not notice any signs or symptoms.

Directions

- do not take more than directed (see Overdose warning)
- do not take more than 12 softgels in any 24-hour period
- adults and children 12 years and older: take 2 softgels every 4 hours
- children under 12 years of age: do not use

Other information

- store between 20-25ºC (68-77ºF)
- avoid excessive heat
- swallow whole; do not crush, chew, or dissolve

Inactive ingredients

FD&C red 40, FD&C yellow #6, gelatin, glycerin, mannitol, polyethylene glycol, povidone, propylene glycol, purified water, sorbitan, sorbitol, titanium dioxide

Questions or comments?

Call 1-877-753-3935 Monday-Friday 9AM-5PM EST

Principal Display Panel

Compare to active ingredients in Maximum Strength Mucinex® Fast-Max® Severe Cold Liquid Gel**

Maximum Strength

Severe Cold

Acetaminophen - Pain reliever, Fever reducer

Dextromethorphan HBr - Cough Suppressant

Guaifenesin- Expectorant

Phenylephrine HCL - Nasal decongestant

MULTI SYMPTOM

- Controls cough
- Thins & loosens mucus
- Relieves nasal & chest congestion
- Relieves aches, fever & sore throat

For Ages 12 +

Alcohol Free

SOFTGELS†

(†Liquid-filled capsules)

*This product is not manufactured or distributed by Reckitt Benckiser, distributor of Maximum Strength Mucinex® Fast-Max® Severe Cold Liquid Gels.

TAMPER EVIDENT: DO NOT USE IF CARTON IS OPENED OR IF BLISTER UNIT IS TORN, BROKEN OR SHOWS ANY SIGNS OF TAMPERING

KEEP OUTER CARTON FOR COMPLETE WARNINGS AND PRODUCT INFORMATION.

Distributed by: CVS Pharmacy, Inc.

One CVS Drive, Woonsocket, RI 02895

CVS.com

Package Label

CVS HEALTH Maximum Strength Severe Cold